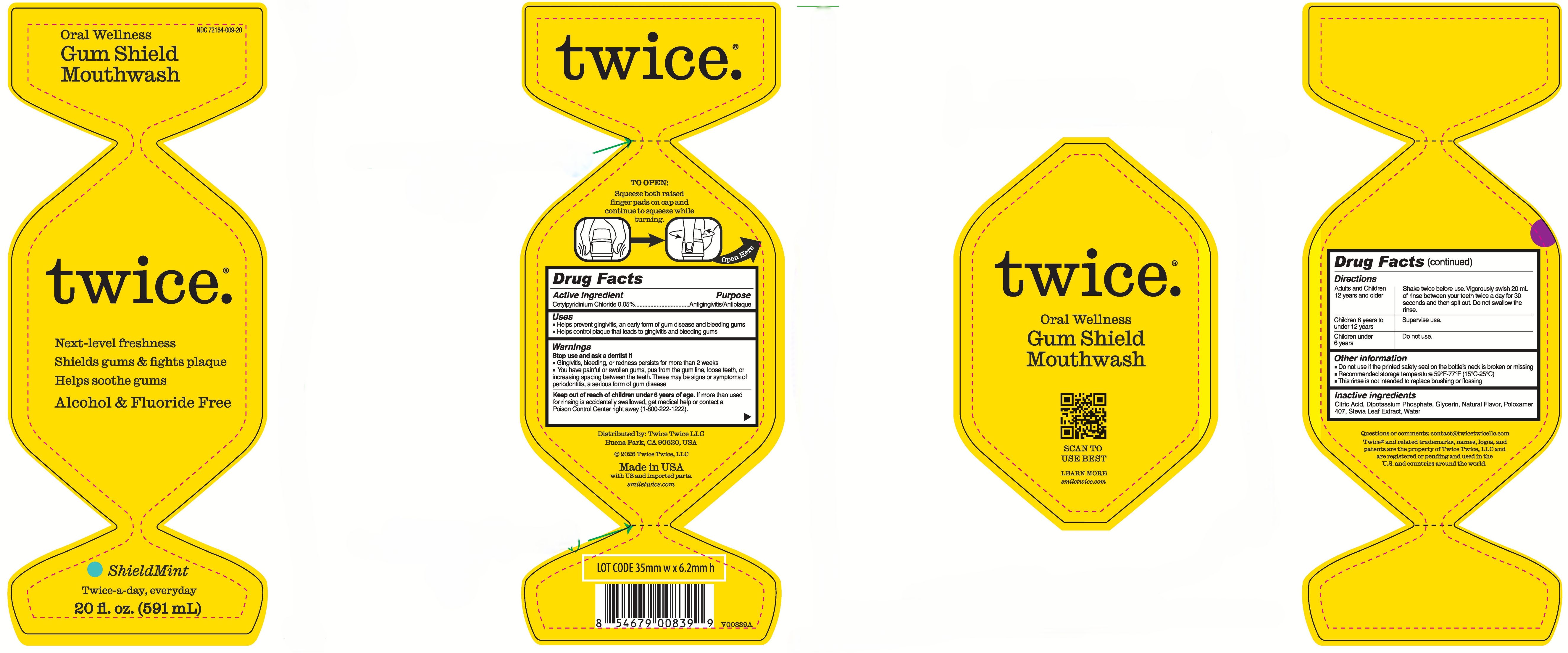 DRUG LABEL: twice. Oral Wellness Gum Shield
NDC: 72164-009 | Form: RINSE
Manufacturer: Twice Twice LLC
Category: otc | Type: HUMAN OTC DRUG LABEL
Date: 20250828

ACTIVE INGREDIENTS: CETYLPYRIDINIUM CHLORIDE 0.5 mg/1 mL
INACTIVE INGREDIENTS: CITRIC ACID; DISODIUM PHOSPHATE; LEMON OIL; WATER; POLOXAMER 407; SPEARMINT OIL; GLYCERIN; STEVIA LEAF

twice. Oral Wellness Gum Shield Mouthwash

Active ingredient

Cetylpyridinium Chloride 0.05%

Purpose

Antigingivitis/Antiplaque mouthrinse

Uses

- Helps prevent gingivitis, an early form of gum disease, and bleeding gums
- Helps control plaque that lead to gingivitis and bleeding gums

Warnings

Stop use and ask a dentist if

- Gingivitis, bleeding, or redness persists for more than 2 weeks
- You have painful or swollen gums, pus from the gum line, loose teeth, or increasing spacing between the teeth. These may be signs or symptoms of periodontitis, a serious form of gum disease

Keep out of reach of children

under 6 years of age. If more than used for rinsing is accidentally swallowed, get medical help or contact a Poison Control Center right away (1-800-222-1222).

Other information

This rinse is not intended to replace brushing or flossing, Do not use if printed safety seal on the bottle's neck is broken or missing, Recommended storage temperature 59°F-77°F (15°C-25°C)

Directions

Adults and children 12 years of age and older: Vigorously swish 20 mL of rinse between your teeth a day for 30 seconds and then split it our. Do not swallow the rinse.

Children 6 years to under 12 yaers: Supervise use.

Children under 6 years: Do not use.

Inactive ingredients

Citric Acid, Disodium Phosphate, Glycerin, Lemon Oil, Poloxamer 407, Spearmint Oil, Stevia Leaf Extract, Water